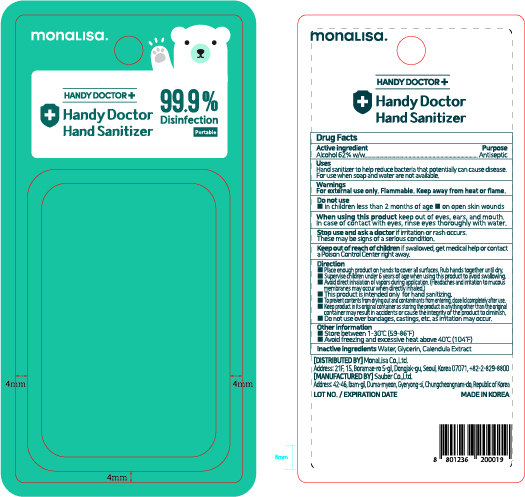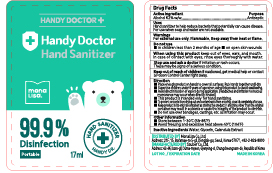 DRUG LABEL: Handy Doctor Hand Sanitizer
NDC: 78880-017 | Form: SPRAY
Manufacturer: Sauber Co.,Ltd.
Category: otc | Type: HUMAN OTC DRUG LABEL
Date: 20210114

ACTIVE INGREDIENTS: ALCOHOL 10.54 mL/17 mL
INACTIVE INGREDIENTS: GLYCERIN; CALENDULA OFFICINALIS WHOLE; WATER

Handy Doctor Hand Sanitizer
78880-017-02

PACKAGE LABEL

[Blister]

[Sticker]